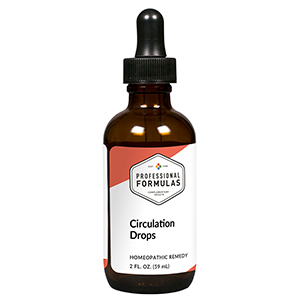 DRUG LABEL: Circulation Drops
NDC: 63083-2013 | Form: LIQUID
Manufacturer: Professional Complementary Health Formulas
Category: homeopathic | Type: HUMAN OTC DRUG LABEL
Date: 20190815

ACTIVE INGREDIENTS: NIACIN 3 [hp_X]/59 mL; NIACINAMIDE 3 [hp_X]/59 mL; VERATRUM ALBUM ROOT 4 [hp_X]/59 mL; EPINEPHRINE 6 [hp_X]/59 mL; CAMPHOR (NATURAL) 6 [hp_X]/59 mL; CAPSICUM 6 [hp_X]/59 mL; STRYCHNOS NUX-VOMICA SEED 6 [hp_X]/59 mL; GINGER 6 [hp_X]/59 mL; ARNICA MONTANA WHOLE 6 [hp_X]/59 mL; HORSE CHESTNUT 12 [hp_X]/59 mL; GOLD 12 [hp_X]/59 mL; GELSEMIUM SEMPERVIRENS ROOT 12 [hp_X]/59 mL; HELODERMA SUSPECTUM WHOLE 12 [hp_X]/59 mL; TOXICODENDRON PUBESCENS LEAF 12 [hp_X]/59 mL; TOBACCO LEAF 12 [hp_X]/59 mL
INACTIVE INGREDIENTS: ALCOHOL; WATER

C13

ACTIVE INGREDIENTS

Niacin 3X
Niacinamide 3X
Veratrum album 4X
Adrenalinum 6X
Camphora 6X
Capsicum annuum 6X
Nux vomica 6X
Zingiber officinale 6X
Arnica montana 6X, 100X
Aesculus hippocastanum 12X
Aurum metallicum 12X
Gelsemium sempervirens 12X
Heloderma 12X
Rhus toxicodendron 12X
Tabacum 12X, 24X

QUESTIONS

Professional Formulas

PO Box 2034 Lake Oswego, OR 97035

INDICATIONS

For the temporary relief of exhaustion, generalized weakness, coldness of extremities, occasional headache, or sporadic leg pain, particularly when walking.*

PURPOSE

*Claims based on traditional homeopathic practice, not accepted medical evidence. Not FDA evaluated.

WARNINGS

Consult a doctor if condition worsens or if symptoms persist. Keep out of the reach of children. In case of overdose, get medical help or contact a poison control center right away. If pregnant or breastfeeding, ask a healthcare professional before use.

Keep out of the reach of children.

PREGNANCY OR BREAST FEEDING

If pregnant or breastfeeding, ask a healthcare professional before use.

DIRECTIONS

Place drops under tongue 30 minutes before/after meals. Adults and children 12 years and over: Take 10 drops up to 3 times per day. Consult a physician for use in children under 12 years of age.

OTHER INFORMATION

Tamper resistant. If seal is broken, do not use. After opening, close container tightly and store at room temperature away from heat.

INACTIVE INGREDIENTS

20% ethanol, purified water.

LABEL

Est 1985

Professional Formulas

Complementary Health

Circulation Drops

Homeopathic Remedy

2 FL. OZ. (59 mL)